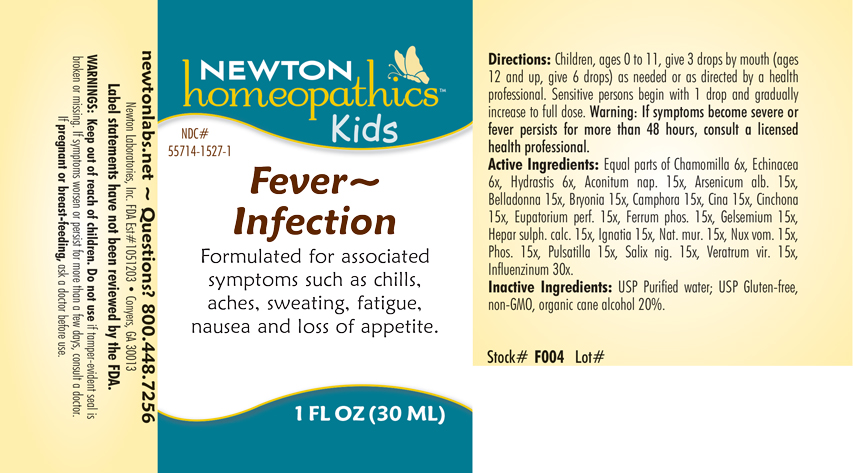 DRUG LABEL: Fever-Infection
NDC: 55714-1527 | Form: LIQUID
Manufacturer: Newton Laboratories, Inc.
Category: homeopathic | Type: HUMAN OTC DRUG LABEL
Date: 20250127

ACTIVE INGREDIENTS: MATRICARIA CHAMOMILLA 6 [hp_X]/1 mL; GELSEMIUM SEMPERVIRENS ROOT 15 [hp_X]/1 mL; GOLDENSEAL 6 [hp_X]/1 mL; ACONITUM NAPELLUS 15 [hp_X]/1 mL; ARSENIC TRIOXIDE 15 [hp_X]/1 mL; ATROPA BELLADONNA 15 [hp_X]/1 mL; BRYONIA ALBA ROOT 15 [hp_X]/1 mL; CAMPHOR (NATURAL) 15 [hp_X]/1 mL; ARTEMISIA CINA PRE-FLOWERING TOP 15 [hp_X]/1 mL; CINCHONA OFFICINALIS BARK 15 [hp_X]/1 mL; EUPATORIUM PERFOLIATUM FLOWERING TOP 15 [hp_X]/1 mL; FERROSOFERRIC PHOSPHATE 15 [hp_X]/1 mL; STRYCHNOS IGNATII SEED 15 [hp_X]/1 mL; SODIUM CHLORIDE 15 [hp_X]/1 mL; STRYCHNOS NUX-VOMICA SEED 15 [hp_X]/1 mL; PHOSPHORUS 15 [hp_X]/1 mL; ANEMONE PULSATILLA 15 [hp_X]/1 mL; SALIX NIGRA BARK 15 [hp_X]/1 mL; VERATRUM VIRIDE ROOT 15 [hp_X]/1 mL; INFLUENZA B VIRUS 30 [hp_X]/1 mL; INFLUENZA A VIRUS 30 [hp_X]/1 mL; CALCIUM SULFIDE 15 [hp_X]/1 mL; ECHINACEA, UNSPECIFIED 6 [hp_X]/1 mL
INACTIVE INGREDIENTS: WATER; ALCOHOL

Fever 1527L

INDICATIONS AND USAGE SECTION

Formuated for associated symptoms such as chills, aches, sweating, fatigue, nausea and loss of appetite.

DOSAGE & ADMINISTRATION SECTION

Directions: Children, ages 0 to 11, give 3 drops by mouth (ages 12 and up, give 6 drops) as needed or a directed by a health professional. Sensitive person begin with 1 drop and gradually increase to full dose.

Warning: If symptoms become severe or fever persists for more than 48 hous, consult a licensed health professional.

OTC - ACTIVE INGREDIENT SECTION

Equal parts of Chamomilla 6x, Echinacea 6x, Hydrastis canadensis 6x, Aconitum napellus 15x, Arsenicum album 15x, Belladonna 15x, Bryonia 15x, Camphora 15x, Cina 15x, Cinchona officinalis 15x, Eupatorium perfoliatum 15x, Ferrum phosphoricum 15x, Gelsemium sempervirens 15x, Hepar sulphuris calcareum 15x, Ignatia amara 15x, Natrum muriaticum 15x, Nux vomica 15x, Phosphorus 15x, Pulsatilla 15x, Salix nigra 15x, Veratrum viride 15x, Influenzinum 30x.

OTC - PURPOSE SECTION

Formulated for associated symptoms such as chills, aches, sweating, fatigue, nausea and loss of appetite.

INACTIVE INGREDIENT SECTION

USP Purified water; USP Gluten-free, non-GMO, organic cane alcohol 20%

QUESTIONS SECTION

newtonlabs.net – Questions? 800.448.7256

Newton Laboratories, Inc. FDA Est # 1051203 - Conyers, GA 30013

WARNINGS SECTION

WARNINGS: Keep out of reach of children. Do not use if tamper-evident seal is broken or missing. If symptoms worsen or persist for more than a few days, consult a doctor. If pregnant or breast-feeding, ask a doctor before use.

OTC - PREGNANCY OR BREAST FEEDING SECTION

If pregnant or breast-feeding, ask a doctor before use.

OTC - KEEP OUT OF REACH OF CHILDREN SECTION

WARNINGS: Keep out of reach of children. Do not use if tamper-evident seal is broken or missing. If symptoms worsen or persist for more than a few days, consult a doctor. If pregnant or breast-feeding, ask a doctor before use.